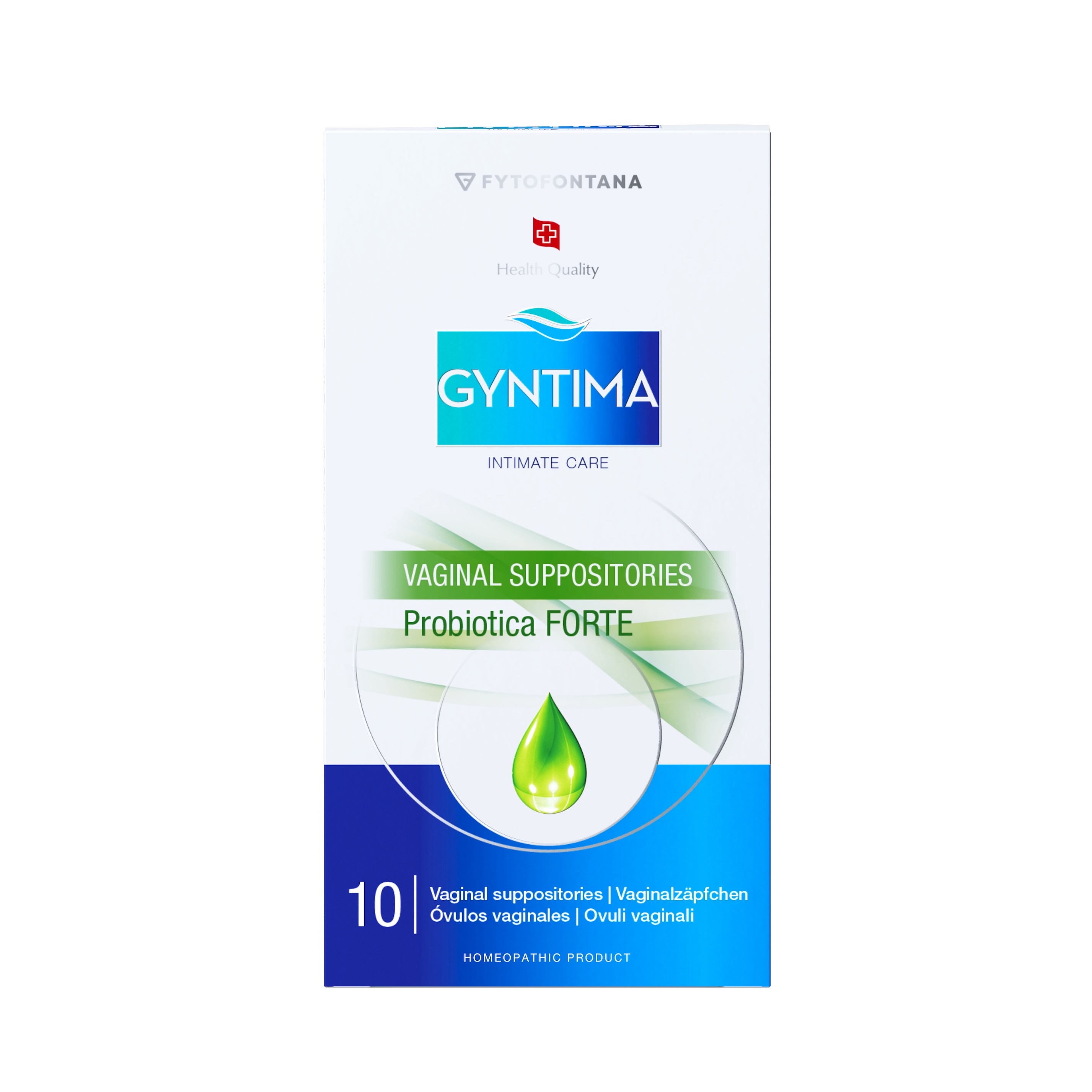 DRUG LABEL: Gyntima Probiotica Forte
NDC: 85401-021 | Form: SUPPOSITORY
Manufacturer: Fytofontana LLC
Category: homeopathic | Type: HUMAN OTC DRUG LABEL
Date: 20250812

ACTIVE INGREDIENTS: SAGE 3 [hp_X]/1 1; LACTIC ACID, DL- 2 [hp_X]/1 1; FOLIC ACID 4 [hp_X]/1 1; TEA TREE OIL 4 [hp_X]/1 1
INACTIVE INGREDIENTS: LACTOSE MONOHYDRATE; PEG-20; PEG-32; SODIUM CHLORIDE; HYDROLYZED CASEIN (ENZYMATIC; 1000 MW); POLYSORBATE 20; MAGNESIUM SULFATE

ACTIVE INGREDIENT

Acidum folicum 4X HPUS – Contributes to the regeneration and repair of vaginal tissues.
Acidum lacticum 2X HPUS – Helps regulate vaginal pH and supports microbiome balance.
Extractum Salviae officinalis 3X HPUS – Helps reduce irritation and supports hydration.
Oleum Melaleucae alternifolia (Tea Tree Oil) 4X HPUS – Traditionally used in homeopathy to support the body’s natural defenses against external imbalances, helping to protect and maintain a healthy vaginal microbiome.

PURPOSE

Supports Vaginal Health

Helps maintain the natural balance of the vaginal microbiome
Supports hydration and elasticity of vaginal tissues
Helps relieve discomfort, irritation, and pH imbalance while providing natural antimicrobial support to help maintain a healthy vaginal environment and support the body's natural defense against vaginal infections.

INDICATIONS AND USAGE

Lowers vaginal pH to create an unfavorable environment for harmful pathogens, while creating the ideal conditions for the body’s own beneficial bacteria, particularly Lactobacillus species, to thrive. Tea tree oil and sage extract provide additional antimicrobial effects, supporting balance and local comfort.

INACTIVE INGREDIENT

PEG 32, Lactosum, Polysorbatum 20, PEG 20, Natrii chloridum, Proteose pepton, Benzalkonii chloridum

Directions for use:

Wash hands and intimate area thoroughly.
Remove the suppository from the blister pack.
Insert deeply into the vagina, preferably in the evening before bed.
Use a sanitary pad, as minor discharge will occur.

Warnings:

Do not use during menstruation.

Do not use during pregnancy.

The vaginal suppository is intended for vaginal use only.

Do not use if the packaging appears damaged.

Do not use after the expiration date indicated on the package.

Keep out of the reach of small children.

Precautions:

Consult your gynecologist when using vaginal preparations along with vaginal contraceptives.

If problems still persist after several days of use, consult your gynecologist.

After gynecological procedures, use only with a physician’s approval.

Any possible discoloration is due to natural plant substances in the product and is not a sign that the preparation is defective.

Regulatory Compliance:

The active ingredients in this product are prepared in accordance with the Homeopathic Pharmacopoeia of the United States (HPUS). These uses are based on traditional homeopathic practice. They have not been reviewed by the Food and Drug Administration.

Keep out of reach of children.
If swallowed, get medical help or contact a Poison Control Center right away.

ASK DOCTOR/PHARMACIST

Consult your gynecologist when using vaginal preparations along with vaginal contraceptives.

If problems still persist after several days of use, consult your gynecologist.

After gynecological procedures, use only with a physician’s approval.

Any possible discoloration is due to natural plant substances in the product and is not a sign that the preparation is defective.

DOSAGE AND ADMINISTRATION

Treatment: 1 suppository daily for 10 consecutive days

Prevention: 1–2 suppositories per week, long-term maintenance

STORAGE AND HANDLING

Store in a cool, dry place away from heat sources and direct sunlight.

Shelf life: 36 months from the date of manufacture.

Distribution:

Fytofontana LLC, 382 NE 191st St PMB 850628 Miami, Florida 33179-3899 USA

Manufacturer:

Herb-Pharma Corporation s.r.o., 935 65 Veľké Ludince, Slovakia under license from Herb-pharma AG Schweiz, Waldmannstrasse 6, 8001 Zürich, Switzerland

For more information visit: www.fytofontana.com